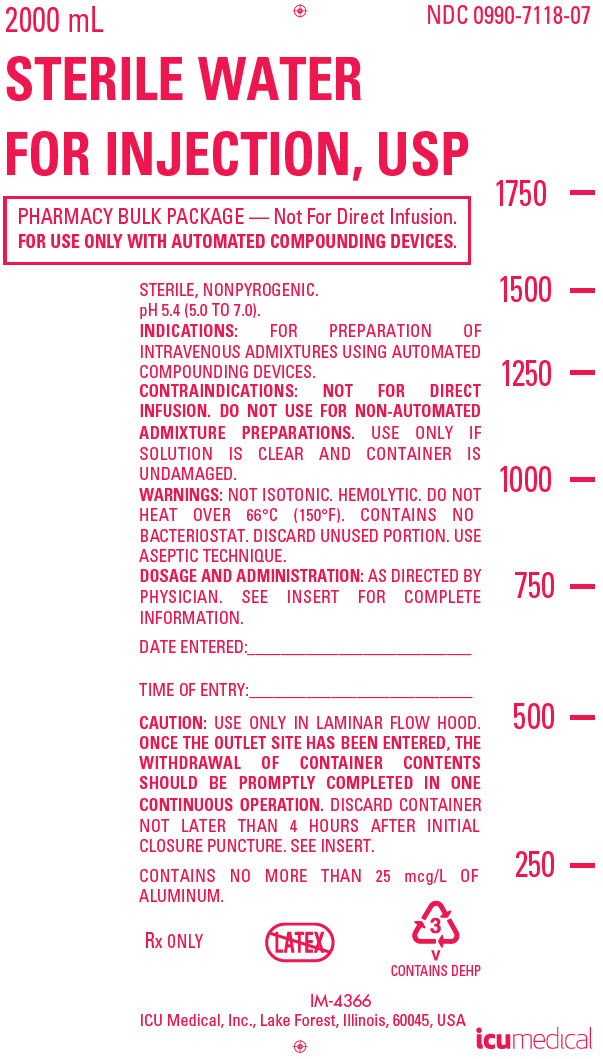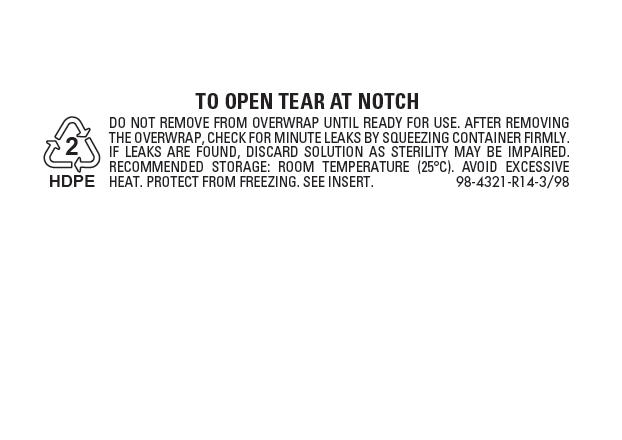 DRUG LABEL: Sterile Water
NDC: 0990-7118 | Form: INJECTION, SOLUTION
Manufacturer: ICU Medical Inc.
Category: prescription | Type: HUMAN PRESCRIPTION DRUG LABEL
Date: 20251029

ACTIVE INGREDIENTS: WATER 1 mL/1 mL

Sterile Water for Injection, USP

BOXED WARNING

Pharmacy Bulk Package — Not for Direct Infusion.

FOR USE ONLY WITH AUTOMATED COMPOUNDING DEVICES.

Flexible Container Rx only

DESCRIPTION

Sterile Water for Injection, USP is a sterile, nonpyrogenic water for injection intended only for dilution purposes. The pH is 5.4 (5.0 to 7.0). The Pharmacy Bulk Package is a sterile dosage form which contains multiple single doses for use only in a pharmacy bulk admixture program.

Sterile Water for Injection, USP contains no bacteriostat, antimicrobial agent or added buffer.

Sterile Water for Injection, USP may be classified as a sterile diluent and pharmaceutical vehicle.

Sterile Water for Injection, USP is chemically designated H2O.

The flexible plastic container is fabricated from a specially formulated polyvinylchloride. Water can permeate from inside the container into the overwrap but not in amounts sufficient to affect the solution significantly. Solutions inside the plastic container also can leach out certain of its chemical components in very small amounts before the expiration period is attained. However, the safety of the plastic has been confirmed by tests in animals according to USP biological standards for plastic containers.

CLINICAL PHARMACOLOGY

Water is an essential constituent of all body tissues and accounts for approximately 70% of total body weight. Average normal adult daily requirement ranges from two to three liters (1.0 to 1.5 liters each for insensible water loss by perspiration and urine production).

Water balance is maintained by various regulatory mechanisms. Water distribution depends primarily on the concentration of electrolytes in the body compartments and sodium (Na^+) plays a major role in maintaining physiologic equilibrium.

INDICATIONS AND USAGE

Sterile Water for Injection, USP in the Pharmacy Bulk Package is indicated for use with automated compounding devices for preparing intravenous admixtures in the pharmacy.

CONTRAINDICATIONS

NOT FOR DIRECT INFUSION. DO NOT USE FOR NON-AUTOMATED ADMIXTURE PREPARATIONS.

WARNINGS

FOR DILUTION ONLY.

Do not heat over 66°C (150°F).

This preparation is solute-free and its entry into the circulation undiluted will cause hemolysis.

Absorption of large amounts of Sterile Water for Injection, USP with additives can cause fluid and/or solute overloading resulting in dilution of serum electrolyte concentrations, overhydration, congested states or pulmonary edema. The risk of dilutional states is inversely proportional to the electrolyte concentrations of administered solutions. The risk of solute overload causing congested states with peripheral and pulmonary edema is directly proportional to the electrolyte concentrations of such solutions.

WARNING: This product contains aluminum that may be toxic. Aluminum may reach toxic levels with prolonged parenteral administration if kidney function is impaired. Premature neonates are particularly at risk because their kidneys are immature, and they require large amounts of calcium and phosphate solutions, which contain aluminum.

Research indicates that patients with impaired kidney function, including premature neonates, who receive parenteral levels of aluminum at greater than 4 to 5 mcg/kg/day accumulate aluminum at levels associated with central nervous system and bone toxicity. Tissue loading may occur at even lower rates of administration.

PRECAUTIONS

Do not use unless water is clear, seal is intact and container is undamaged.

Aseptic technique is essential with the use of sterile preparations for compounding admixtures.

Discard container within 4 hours of entering closure.

ADVERSE REACTIONS

Accidental contamination from careless technique may transmit infection.

Should any adverse reaction occur, evaluate the patient, institute appropriate therapeutic countermeasures and save the remainder of the fluid for examination, if deemed necessary.

DOSAGE AND ADMINISTRATION

Sterile Water for Injection, USP in the 2000 mL flexible Pharmacy Bulk Package is designed for use with automated compounding devices for preparing intravenous admixtures. Dosages will be in accordance with the recommendation of the prescribing physician.

Sterile Water for Injection, USP is not intended for direct infusion. Admixtures should be made by or under the direction of a pharmacist using strict aseptic technique under a laminar flow hood. Compounded admixtures may be stored under refrigeration for up to 24 hours. Administration of admixtures should be completed within 24 hours after removal from refrigeration.

Drug Interactions

The Pharmacy Bulk Package is intended only for use in the preparation of sterile, intravenous admixtures using automated compounding devices.

Additives may be incompatible with the fluid withdrawn from this container. Consult with pharmacist, if available. When compounding admixtures, use aseptic technique, mix thoroughly and do not store.

Parenteral drug products should be inspected visually for particulate matter and discoloration prior to administration, whenever solution container permits. See PRECAUTIONS.

Some opacity of the plastic due to moisture absorption during the sterilization process may be observed. This is normal and does not affect the solution quality or safety. The opacity will diminish gradually.

Recommended Directions for Use of the Pharmacy Bulk Package

Use Aseptic Technique

1. During use, container must be stored, and all manipulations performed, in an appropriate laminar flow hood.

2. Remove cover from outlet port at bottom of container.

3. Insert piercing pin of transfer set and suspend unit in a laminar flow hood. Insertion of a piercing pin into the outlet port should be performed only once in a Pharmacy Bulk Package solution. Once the outlet site has been entered, the withdrawal of container contents should be completed promptly in one continuous operation. Should this not be possible, a maximum time of 4 hours from transfer set pin or implement insertion is permitted to complete fluid transfer operations; i.e., discard container no later than 4 hours after initial closure puncture.

4. Sequentially dispense aliquots of Sterile Water for Injection, USP into I.V. containers using appropriate transfer set. During fluid transfer operations, the Pharmacy Bulk Package should be maintained under the storage conditions recommended in the labeling.

HOW SUPPLIED

Sterile Water for Injection, USP is supplied in 2000 mL flexible Pharmacy Bulk Packages.

NDC No. | Product | Container Size (mL)
0409-7118-07 | Sterile Water for Injection, USP | 2000
0990-7118-07 | Sterile Water for Injection, USP | 2000

ICU Medical is transitioning NDC codes from the "0409" to a "0990" labeler code. Both codes are expected to be in the market for a period of time.

Store at 20 to 25°C (68 to 77°F). [See USP Controlled Room Temperature.] Protect from freezing.

Patent 4,368,765

Revised: July, 2018

ICU Medical, Inc., Lake Forest, Illinois, 60045, USA

EN-4665

PRINCIPAL DISPLAY PANEL - 2000 mL Bag Label

2000 mL
NDC 0990-7118-07

STERILE WATER
FOR INJECTION, USP

PHARMACY BULK PACKAGE — Not For Direct Infusion.
FOR USE ONLY WITH AUTOMATED COMPOUNDING DEVICES.

STERILE, NONPYROGENIC.
pH 5.4 (5.0 TO 7.0).

INDICATIONS: FOR PREPARATION OF
INTRAVENOUS ADMIXTURES USING AUTOMATED
COMPOUNDING DEVICES.

CONTRAINDICATIONS: NOT FOR DIRECT
INFUSION. DO NOT USE FOR NON-AUTOMATED
ADMIXTURE PREPARATIONS. USE ONLY IF
SOLUTION IS CLEAR AND CONTAINER IS
UNDAMAGED.

WARNINGS: NOT ISOTONIC. HEMOLYTIC. DO NOT
HEAT OVER 66°C (150°F). CONTAINS NO
BACTERIOSTAT. DISCARD UNUSED PORTION. USE
ASEPTIC TECHNIQUE.

DOSAGE AND ADMINISTRATION: AS DIRECTED BY
PHYSICIAN. SEE INSERT FOR COMPLETE
INFORMATION.

DATE ENTERED:___________________________

TIME OF ENTRY:___________________________

CAUTION: USE ONLY IN LAMINAR FLOW HOOD.
ONCE THE OUTLET SITE HAS BEEN ENTERED, THE
WITHDRAWAL OF CONTAINER CONTENTS
SHOULD BE PROMPTLY COMPLETED IN ONE
CONTINUOUS OPERATION. DISCARD CONTAINER
NOT LATER THAN 4 HOURS AFTER INITIAL
CLOSURE PUNCTURE. SEE INSERT.

CONTAINS NO MORE THAN 25 mcg/L OF
ALUMINUM.

Rx ONLY

3
V
CONTAINS DEHP

IM-4366

ICU Medical, Inc., Lake Forest, Illinois, 60045, USA

icumedical

PRINCIPAL DISPLAY PANEL - 2000 mL Bag Overwrap

TO OPEN TEAR AT NOTCH

2
HDPE

DO NOT REMOVE FROM OVERWRAP UNTIL READY FOR USE. AFTER REMOVING
THE OVERWRAP, CHECK FOR MINUTE LEAKS BY SQUEEZING CONTAINER FIRMLY.
IF LEAKS ARE FOUND, DISCARD SOLUTION AS STERILITY MAY BE IMPAIRED.
RECOMMENDED STORAGE: ROOM TEMPERATURE (25°C). AVOID EXCESSIVE
HEAT. PROTECT FROM FREEZING. SEE INSERT.
98-4321-R14-3/98